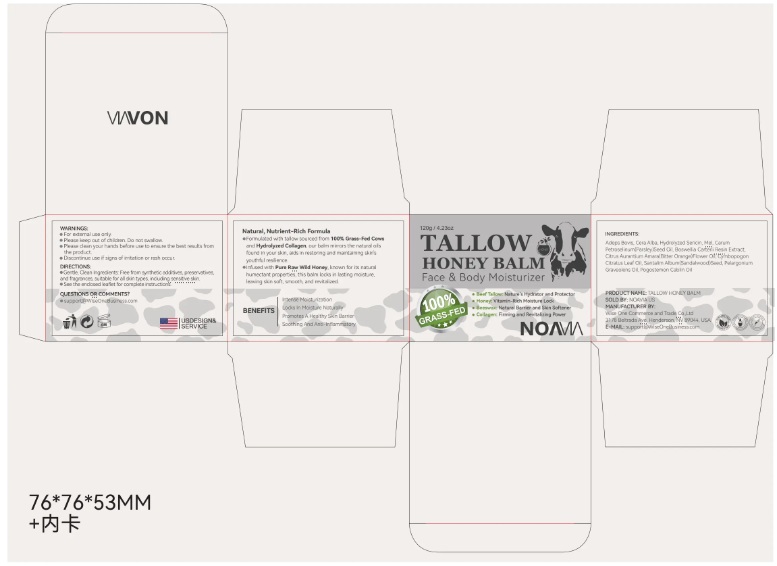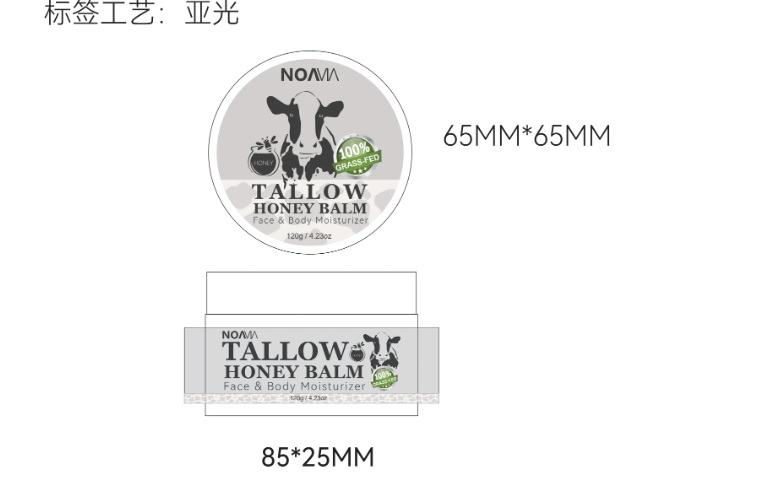 DRUG LABEL: NOAVIA Honey beef fat cream
NDC: 85212-0012 | Form: CREAM
Manufacturer: Beijing JUNGE Technology Co., Ltd.
Category: otc | Type: HUMAN OTC DRUG LABEL
Date: 20250226

ACTIVE INGREDIENTS: BEESWAX 5 g/100 mL; ADEPS BOVIS 71.7 g/100 mL; HONEY 5 g/100 mL
INACTIVE INGREDIENTS: PELARGONIUM GRAVEOLENS WHOLE 1 mL/100 mL; GERANIOL 0.1 mL/100 mL; SANTALUM ALBUM (SANDALWOOD) SEED OIL 2 mL/100 mL; CARUM PETROSELINUM (PARSLEY) SEED OIL 5 mL/100 mL; CITRIC ACID 1 mL/100 mL; LINALOOL 1 mL/100 mL; CYMBOPOGON CITRATUS LEAF OIL 2 mL/100 mL; BOSWELLIA CARTERII OIL 2 mL/100 mL; FARNESOL 1 mL/100 mL; CITRONELLAL 0.1 mL/100 mL; CITRONELLOL 0.1 mL/100 mL; CITRUS AURANTIUM AMARA (BITTER ORANGE) FLOWER OIL 2 mL/100 mL; POGOSTEMON CABLIN OIL 1 mL/100 mL

WARNINGS

For external use only.

Please keep out of children.

Do not swwallow.

Please clean your hands before use to ensure the best results from the product.
Discontinue use if signs of irritation or rash oocur.

INDICATIONS AND USAGE

Gentle, Clean Ingredients: Free from synthetic addlitives, preservatiwes and fragrances, suitable for all skin types, incudng sensitive skin.

See the enclosed leaflet for complete instructions.

QUESTIONS

support@WiseOneBusiness.com

ACTIVE INGREDIENT

ADEPS BOVIS,CERA ALBA,MEL

Keep out of reach of children. If swallowed, get medical help or contact a Poison Control Center right away

PRECAUTIONS

After using the product if irritation or rash appears,discontinue use.If irritation or
rash persists.consult your doctor.

INACTIVE INGREDIENT

CARUM PETROSELINUM (PARSLEY) SEED OIL
BOSWELLIA CARTERII RESIN EXTRACT
CITRUS AURANTIUM AMARA (BITTER ORANGE) FLOWER OIL
CYMBOPOGON CITRATUS LEAF OIL
SANTALUM ALBUM (SANDALWOOD) SEED OIL
PELARGONIUM GRAVEOLENS OIL
POGOSTEMON CABLIN OIL
CITRIC ACID
LINALOOL
FARNESOL
CITRONELLAL
GERANIOL
CITRONELLOL

DOSAGE AND ADMINISTRATION

120ml/4.2fl.oz

PURPOSE

Moisturizing